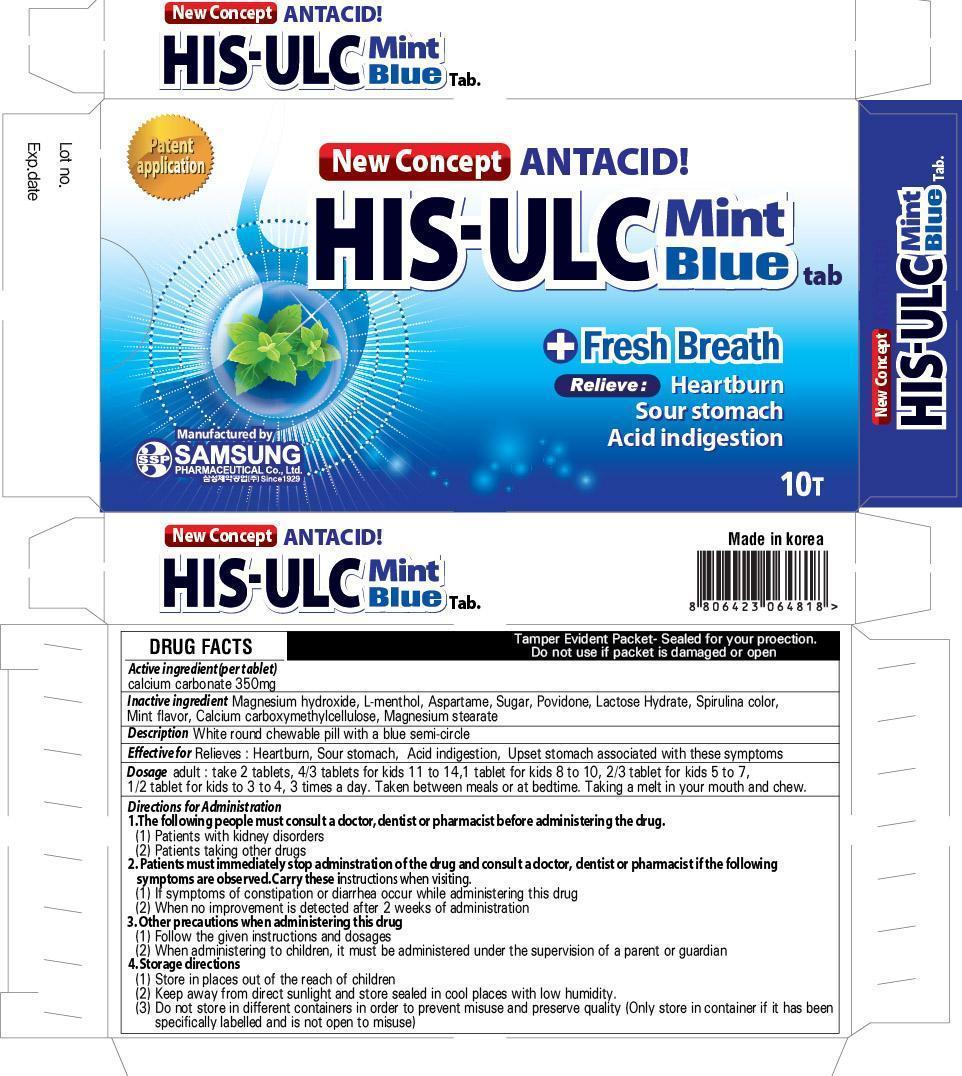 DRUG LABEL: HIS ULC MINT BLUE
NDC: 49789-060 | Form: TABLET, CHEWABLE
Manufacturer: SAMSUNG PHARM IND. CO., LTD.
Category: otc | Type: HUMAN OTC DRUG LABEL
Date: 20130403

ACTIVE INGREDIENTS: Calcium carbonate 350 mg/492 mg
INACTIVE INGREDIENTS: magnesium hydroxide; Aspartame

ACTIVE INGREDIENT

Active ingredient: Calcium carbonate 350mg

INACTIVE INGREDIENT

Inactive ingredients:
Magnesium hydroxide, L-menthol, Aspartame, Sugar, Povidone, Lactose Hydrate, Spirulina color, Mint flavor, Calcium carboxymethylcellulose, Magnesium stearate

PURPOSE

Effective for: Relieves:Heartburn, Sour stomach, Acid indigestion, Upset stomach associated with these symptoms

WARNINGS

1. The following people must consult a doctor, dentist or pharmacist before administering the drug.
(1) Patients with kidney disorders
(2) Patients taking other drugs

2. Patients must immediately stop adminstration of the drug and consult a doctor, dentist or pharmacist if the following symptoms are observed. Carry these instructions when visiting.
(1) If symptoms of constipation or diarrhea occur while administering this drug
(2) When no improvement is detected after 2 weeks of administration

3. Other precautions when administering this drug
(1) Follow the given instructions and dosages
(2) When administering to children, it must be administered under the supervision of a parent or guardian

4. Storage directions
(1) Store in places out of the reach of children
(2) Keep away from direct sunlight and store sealed in cool places with low humidity.
(3) Do not store in different containers in order to prevent misuse and preserve quality (Only store in container if it has been specifically labelled and is not open to misuse)

KEEP OUT OF REACH OF CHILDREN

INDICATIONS AND USAGE

adult :take 2 tablets, 4/3 tablets for kids 11 to 14, 1 tablet for kids 8 to 10, 2/3 tablet for kids 5 to 7, 1/2 tablet for kids to 3 to 4, 3 times a day. Taken between meals or at bedtime
Taking a melt in your mouth and chew.

DOSAGE AND ADMINISTRATION

adult :take 2 tablets, 4/3 tablets for kids 11 to 14, 1 tablet for kids 8 to 10, 2/3 tablet for kids 5 to 7, 1/2 tablet for kids to 3 to 4, 3 times a day. Taken between meals or at bedtime
Taking a melt in your mouth and chew.